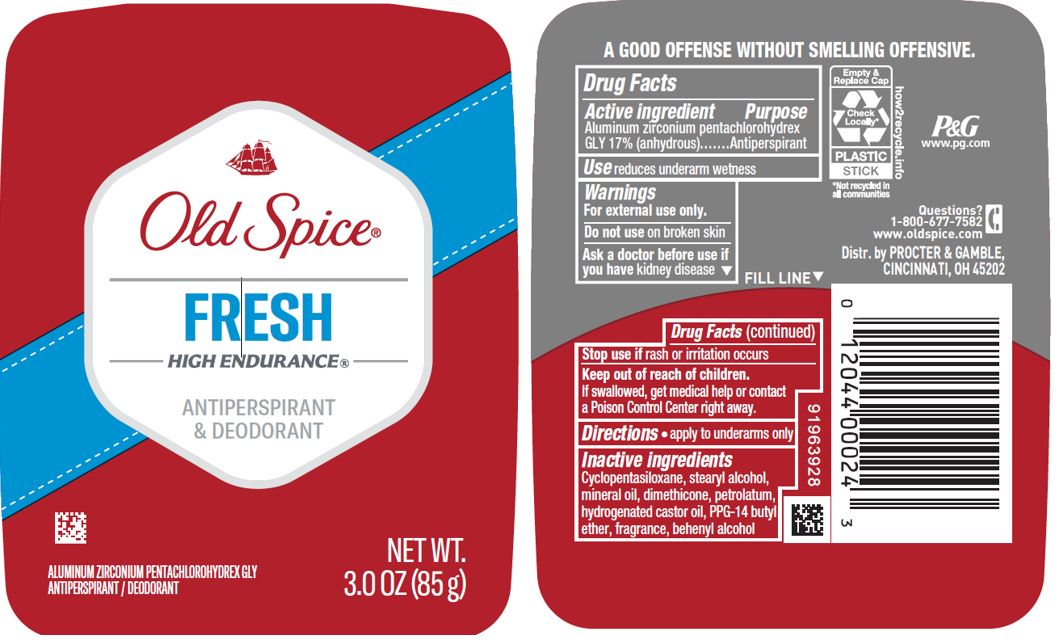 DRUG LABEL: Old Spice Fresh
NDC: 69423-609 | Form: STICK
Manufacturer: The Procter & Gamble Manufacturing Company
Category: otc | Type: HUMAN OTC DRUG LABEL
Date: 20251218

ACTIVE INGREDIENTS: ALUMINUM ZIRCONIUM PENTACHLOROHYDREX GLY 17 g/100 g
INACTIVE INGREDIENTS: HYDROGENATED CASTOR OIL; STEARYL ALCOHOL; PPG-14 BUTYL ETHER; PETROLATUM; MINERAL OIL; DOCOSANOL; DIMETHICONE; CYCLOMETHICONE 5

Old Spice® Fresh High Endurance® (new active)

Drug Facts

Active ingredient

Aluminum zirconium pentachlorohydrex Gly 17% (anhydrous)

Purpose

Antiperspirant

Use

reduces underarm wetness

Warnings

For external use only.

Do not use on broken skin

Ask a doctor before use if you have kidney disease

Stop use if rash or irritation occurs

Keep out of reach of children. If swallowed, get medical help or contact a Poison Control Center right away.

Directions

- apply to underarms only

Inactive ingredients

cyclopentasiloxane, stearyl alcohol, mineral oil, dimethicone, petrolatum, hydrogenated castor oil, PPG-14 butyl ether, fragrance, behenyl alcohol

Questions?

1-800-677-7582

Dist. by PROCTER & GAMBLE, CINCINNATI, OH 45202.

PRINCIPAL DISPLAY PANEL - 85 g Canister Label

Old Spice®

FRESH
HIGH ENDURANCE®

ANTIPERSPIRANT
& DEODORANT

Aluminum Zirconium Pentachlorohydrex Gly
ANTIPERSPIRANT/DEODORANT

NET WT. 3.0 OZ (85 g)